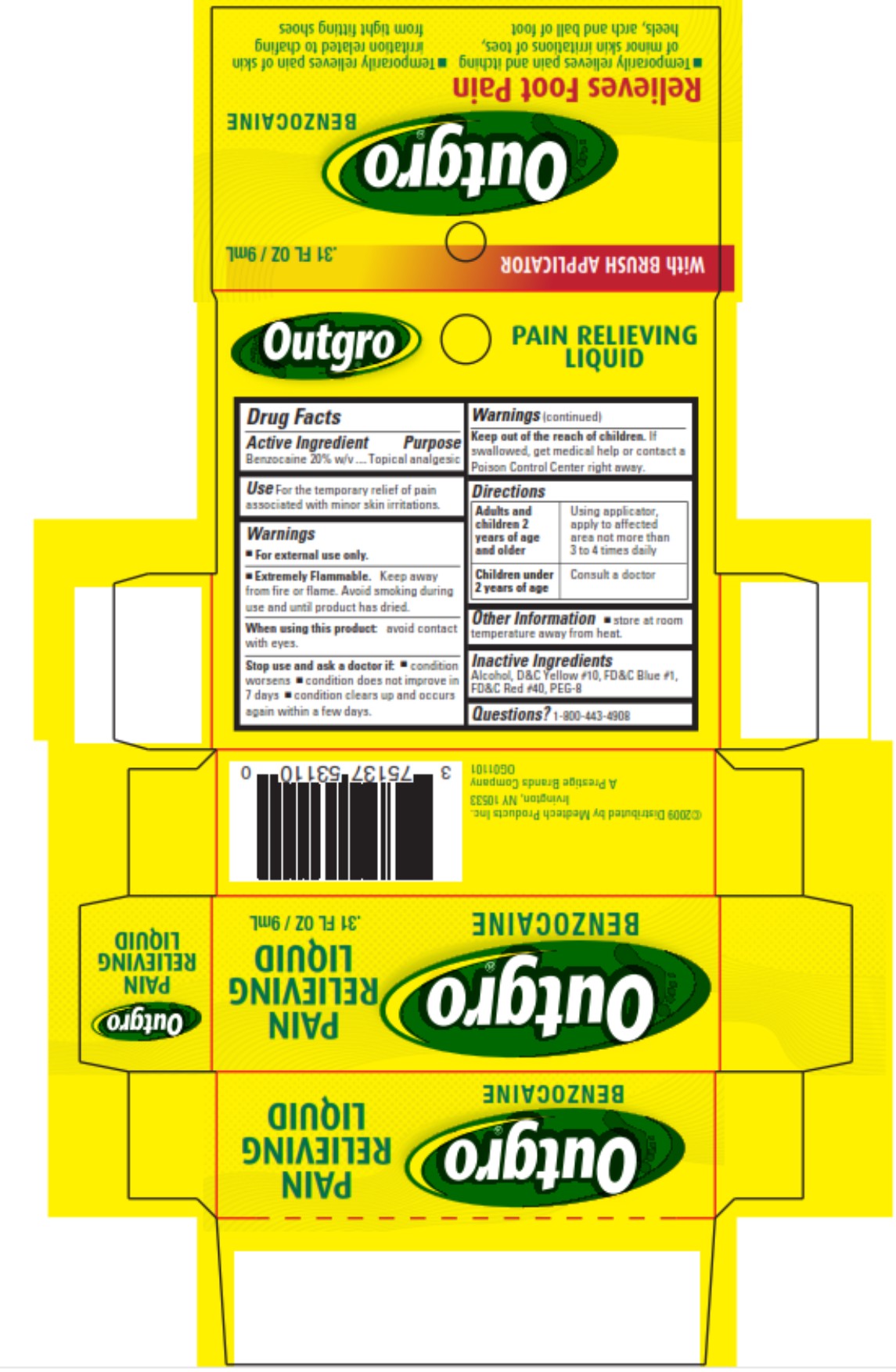 DRUG LABEL: Outgro
NDC: 63029-531 | Form: LIQUID
Manufacturer: Medtech Products Inc.
Category: otc | Type: HUMAN OTC DRUG LABEL
Date: 20241025

ACTIVE INGREDIENTS: BENZOCAINE 18.6 g/100 mL
INACTIVE INGREDIENTS: ALCOHOL; D&C YELLOW NO. 10; FD&C BLUE NO. 1; FD&C RED NO. 40; POLYETHYLENE GLYCOL 400

Outgro

Outgro®

PAIN RELIEVING LIQUID

Drug Facts

Active Ingredient

Benzocaine 20% w/v

Purpose

Topical analgesic

Use

For the temporary relief of pain associated with minor skin irritations.

Warnings

■ For external use only.

■ Extremely Flammable. Keep away from fire or flame. Avoid smoking during use and until product has dried.

When using this product:

avoid contact with eyes.

Stop use and ask a doctor if:

■ condition worsens ■ condition does not improve in 7 days ■ condition clears up and occurs again within a few days.

Keep out of the reach of children.

If swallowed, get medical help or contact a Poison Control Center right away.

Directions

Adults and children 2 years of age and older | Using applicator, apply to affected area not more than 3 to 4 times daily
Children under 2 years of age | Consult a doctor

Other Information

■ store at room temperature away from heat.

Inactive Ingredients

Alcohol, D&C Yellow #10, FD&C Blue #1, FD&C Red #40, PEG-8

Questions?

1-800-443-4908

Principal Display Panel

Outgro
BENZOCAINE
PAIN RELIEVING
LIQUID
.31 FL OZ/ 9 mL